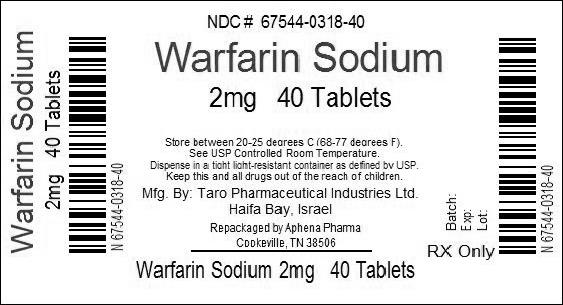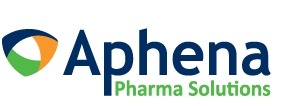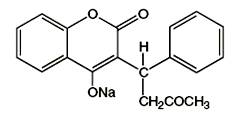 DRUG LABEL: Warfarin Sodium
NDC: 67544-318 | Form: TABLET
Manufacturer: Aphena Pharma Solutions - Tennessee, LLC
Category: prescription | Type: HUMAN PRESCRIPTION DRUG LABEL
Date: 20140506

ACTIVE INGREDIENTS: WARFARIN SODIUM 2 mg/1 1
INACTIVE INGREDIENTS: Anhydrous lactose; STARCH, CORN; magnesium stearate; FD&C BLUE NO. 2; FD&C RED NO. 40

Warfarin Sodium
Tablets, USP
Crystalline

BOXED WARNING

BLEEDING WARNING: Warfarin sodium can cause major or fatal bleeding. Bleeding is more likely to occur during the starting period and with a higher dose (resulting in a higher INR). Risk factors for bleeding include high intensity of anticoagulation (INR >4.0), age ≥65, highly variable INRs, history of gastrointestinal bleeding, hypertension, cerebrovascular disease, serious heart disease, anemia, malignancy, trauma, renal insufficiency, concomitant drugs (see PRECAUTIONS), and long duration of warfarin therapy. Regular monitoring of INR should be performed on all treated patients. Those at high risk of bleeding may benefit from more frequent INR monitoring, careful dose adjustment to desired INR, and a shorter duration of therapy. Patients should be instructed about prevention measures to minimize risk of bleeding and to report immediately to physicians signs and symptoms of bleeding (see PRECAUTIONS: Information for Patients).

DESCRIPTION

Crystalline warfarin sodium is an anticoagulant which acts by inhibiting vitamin K-dependent coagulation factors. Chemically, it is 3-(α-acetonylbenzyl)-4-hydroxycoumarin sodium salt and is a racemic mixture of theR- andS-enantiomers. Crystalline warfarin sodium is an isopropanol clathrate. The crystallization of warfarin sodium virtually eliminates trace impurities present in amorphous warfarin. Its empirical formula is C19H15NaO4, and its structural formula may be represented by the following:

Crystalline warfarin sodium occurs as a white, odorless, crystalline powder, is discolored by light and is very soluble in water; freely soluble in alcohol; very slightly soluble in chloroform and in ether.

Warfarin Sodium Tablets, USP for oral use also contain:

All strengths: | Anhydrous lactose, corn starch and magnesium stearate
1 mg: | D&C red #6 Barium Lake.
2 mg: | FD&C blue #2 Aluminum Lake, FD&C red #40 Aluminum Lake.
2.5 mg: | FD&C blue #2 Aluminum Lake, D&C yellow #10 Aluminum Lake.
3 mg: | FD&C blue #2 Aluminum Lake, FD&C red #40 Aluminum Lake, D&C yellow #10 Aluminum Lake.
4 mg: | FD&C blue #1 Aluminum Lake.
5 mg: | D&C yellow #10 Aluminum Lake, D&C red #6 Barium Lake.
6 mg: | D&C yellow #10 Aluminum Lake, FD&C blue #2 Aluminum Lake.
7.5 mg: | D&C yellow #10 Aluminum Lake.
10 mg: | Dye Free

CLINICAL PHARMACOLOGY

Warfarin sodium tablets, USP and other coumarin anticoagulants act by inhibiting the synthesis of vitamin K dependent clotting factors, which include Factors II, VII, IX and X, and the anticoagulant proteins C and S. Half-lives of these clotting factors are as follows: Factor II - 60 hours, VII - 4-6 hours, IX - 24 hours, and X - 48-72 hours. The half-lives of proteins C and S are approximately 8 hours and 30 hours, respectively. The resultantin vivoeffect is a sequential depression of Factor VII, Protein C, Factor IX, Protein S, and Factor X and II activities. Vitamin K is an essential cofactor for the post ribosomal synthesis of the vitamin K dependent clotting factors. The vitamin promotes the biosynthesis of γ-carboxyglutamic acid residues in the proteins which are essential for biological activity.

Mechanism of Action

Warfarin is thought to interfere with clotting factor synthesis by inhibition of the C1 subunit of the vitamin K epoxide reductase (VKORC1) enzyme complex, thereby reducing the regeneration of vitamin K1 epoxide. The degree of depression is dependent upon the dosage administered and, in part, by the patient's VKORC1 genotype. Therapeutic doses of warfarin decrease the total amount of the active form of each vitamin K dependent clotting factor made by the liver by approximately 30% to 50%.

An anticoagulation effect generally occurs within 24 hours after drug administration. However, peak anticoagulant effect may be delayed 72 to 96 hours. The duration of action of a single dose of racemic warfarin is 2 to 5 days. The effects of warfarin sodium tablets, USP may become more pronounced as effects of daily maintenance doses overlap. Anticoagulants have no direct effect on an established thrombus, nor do they reverse ischemic tissue damage. However, once a thrombus has occurred, the goal of anticoagulant treatment is to prevent further extension of the formed clot and prevent secondary thromboembolic complications which may result in serious and possibly fatal sequelae.

Pharmacokinetics

Warfarin sodium tablets, USP is a racemic mixture of theR- andS-enantiomers. TheS-enantiomer exhibits 2-5 times more anticoagulant activity than theR-enantiomer in humans, but generally has a more rapid clearance.

Absorption

Warfarin sodium tablets, USP is essentially completely absorbed after oral administration with peak concentration generally attained within the first 4 hours.

Distribution

There are no differences in the apparent volumes of distribution after intravenous and oral administration of single doses of warfarin solution. Warfarin distributes into a relatively small apparent volume of distribution of about 0.14 liter/kg. A distribution phase lasting 6 to 12 hours is distinguishable after rapid intravenous or oral administration of an aqueous solution. Using a one compartment model, and assuming complete bioavailability, estimates of the volumes of distribution of R- and S-warfarin are similar to each other and to that of the racemate. Concentrations in fetal plasma approach the maternal values, but warfarin has not been found in human milk (seeWARNINGS - Lactation). Approximately 99% of the drug is bound to plasma proteins.

Metabolism

The elimination of warfarin is almost entirely by metabolism. Warfarin sodium tablets, USP is stereoselectively metabolized by hepatic microsomal enzymes (cytochrome P-450) to inactive hydroxylated metabolites (predominant route) and by reductases to reduced metabolites (warfarin alcohols). The warfarin alcohols have minimal anticoagulant activity. The metabolites are principally excreted into the urine; and to a lesser extent into the bile. The metabolites of warfarin that have been identified include dehydrowarfarin, two diastereoisomer alcohols, 4'-, 6-, 7-, 8- and 10-hydroxywarfarin. The cytochrome P-450 isozymes involved in the metabolism of warfarin include 2C9, 2C19, 2C8, 2C18, 1A2, and 3A4. 2C9 is likely to be the principal form of human liver P-450 which modulates the in vivo anticoagulant activity of warfarin.

TheS-enantiomer of warfarin is mainly metabolized to 7-hydroxywarfarin by CYP2C9, a polymorphic enzyme. The variant alleles CYP2C9*2 and CYP2C9*3 result in decreased in vitro CYP2C9 enzymatic 7-hydroxylation of S-warfarin. The frequencies of these alleles in Caucasians are approximately 11% and 7% for CYP2C9*2 and CYP2C9*3, respectively^1. Patients with one or more of these variant CYP2C9 alleles have decreased S-warfarin clearance (Table 1).^2

Table 1. Relationship Between S-Warfarin Clearance and CYP2C9 Genotype in Caucasian Patients
CYP2C9 Genotype | N | S-Warfarin Clearance/Lean Body Weight (mL/min/kg) Mean (SD)a
*1/*1 | 118 | 0.065 (0.025)b
*1/*2 or *1/*3 | 59 | 0.041 (0.021)b
*2/*2, *2/*3, or *3/*3 | 11 | 0.020 (0.011)b
Total | 188
aSD=standard deviation.
bp<0.001. Pairwise comparisons indicated significant differences among all 3 genotypes.

Other CYP2C9 alleles associated with reduced enzymatic activity occur at lower frequencies, including *5, *6, and *11 alleles in populations of African ancestry and *5, *9 and *11 alleles in Caucasians.

Pharmacogenomics

A meta-analysis of 9 qualified studies including 2775 patients (99% Caucasian) was performed to examine the clinical outcomes associated with CYP2C9 gene variants in warfarin-treated patients.^3In this meta-analysis, 3 studies assessed bleeding risks and 8 studies assessed daily dose requirements. The analysis suggested an increased bleeding risk for patients carrying either the CYP2C9*2 or CYP2C9*3 alleles. Patients carrying at least one copy of the CYP2C9*2 allele required a mean daily warfarin dose that was 17% less than the mean daily dose for patients homozygous for the CYP2C9*1 allele. For patients carrying at least one copy of the CYP2C9*3 allele, the mean daily warfarin dose was 37% less than the mean daily dose for patients homozygous for the CYP2C9*1 allele.

In an observational study, the risk of achieving INR >3 during the first 3 weeks of warfarin therapy was determined in 219 Swedish patients retrospectively grouped by CYP2C9 genotype. The relative risk of over anticoagulation as measured by INR >3 during the first 2 weeks of therapy was approximately doubled for those patients classified as *2 or *3 compared to patients who were homozygous for the *1 allele.^4

Warfarin reduces the regeneration of vitamin K from vitamin K epoxide in the vitamin K cycle, through inhibition of vitamin K epoxide reductase (VKOR), a multiprotein enzyme complex. Certain single nucleotide polymorphisms in the VKORC1 gene (especially the –1639G>A allele) have been associated with lower dose requirements for warfarin. In 201 Caucasian patients treated with stable warfarin doses, genetic variations in the VKORC1 gene were associated with lower warfarin doses. In this study, about 30% of the variance in warfarin dose could be attributed to variations in the VKORC1 gene alone; about 40% of the variance in warfarin dose could be attributed to variations in VKORC1 and CYP2C9 genes combined. About 55% of the variability in warfarin dose could be explained by the combination of VKORC1 and CYP2C9 genotypes, age, height, body weight, interacting drugs, and indication for warfarin therapy in Caucasian patients.^5Similar observations have been reported in Asian patients.^6,7

Excretion

The terminal half-life of warfarin after a single dose is approximately one week; however, the effective half-life ranges from 20 to 60 hours, with a mean of about 40 hours. The clearance of R-warfarin is generally half that of S-warfarin, thus as the volumes of distribution are similar, the half-life of R-warfarin is longer than that of S-warfarin. The half-life of R-warfarin ranges from 37 to 89 hours, while that of S-warfarin ranges from 21 to 43 hours. Studies with radiolabeled drug have demonstrated that up to 92% of the orally administered dose is recovered in urine. Very little warfarin is excreted unchanged in urine. Urinary excretion is in the form of metabolites.

Elderly

Patients 60 years or older appear to exhibit greater than expected PT/INR response to the anticoagulant effects of warfarin. The cause of the increased sensitivity to the anticoagulant effects of warfarin in this age group is unknown. This increased anticoagulant effect from warfarin may be due to a combination of pharmacokinetic and pharmacodynamic factors. Racemic warfarin clearance may be unchanged or reduced with increasing age. Limited information suggests there is no difference in the clearance of S-warfarin in the elderly versus young subjects. However, there may be a slight decrease in the clearance of R-warfarin in the elderly as compared to the young. Therefore, as patient age increases, a lower dose of warfarin is usually required to produce a therapeutic level of anticoagulation.

Asians

Asian patients may require lower initiation and maintenance doses of warfarin. One non-controlled study conducted in 151 Chinese outpatients reported a mean daily warfarin requirement of 3.3±1.4 mg to achieve an INR of 2 to 2.5. These patients were stabilized on warfarin for various indications. Patient age was the most important determinant of warfarin requirement in Chinese patients with a progressively lower warfarin requirement with increasing age.

Renal Dysfunction

Renal clearance is considered to be a minor determinant of anticoagulant response to warfarin. No dosage adjustment is necessary for patients with renal failure.

Hepatic Dysfunction

Hepatic dysfunction can potentiate the response to warfarin through impaired synthesis of clotting factors and decreased metabolism of warfarin.

The administration of warfarin via the intravenous (IV) route should provide the patient with the same concentration of an equal oral dose, but maximum plasma concentration will be reached earlier. However, the full anticoagulant effect of a dose of warfarin may not be achieved until 72-96 hours after dosing, indicating that the administration of IV warfarin should not provide any increased biological effect or earlier onset of action.

CLINICAL TRIALS

Atrial Fibrillation (AF)

In five prospective randomized controlled clinical trials involving 3711 patients with non-rheumatic AF, warfarin significantly reduced the risk of systemic thromboembolism including stroke (See Table 2). The risk reduction ranged from 60% to 86% in all except one trial (CAFA: 45%) which stopped early due to published positive results from two of these trials. The incidence of major bleeding in these trials ranged from 0.6 to 2.7% (see table 2). Meta-analysis findings of these studies revealed that the effects of warfarin in reducing thromboembolic events including stroke were similar at either moderately high INR (2.0-4.5) or low INR (1.4-3.0). There was a significant reduction in minor bleeds at the low INR. Similar data from clinical studies in valvular atrial fibrillation patients are not available.

TABLE 2 CLINICAL STUDIES OF WARFARIN IN NON-RHEUMATIC AF PATIENTS*
Study | N |  |  |  | Thromboembolism |  | % Major Bleeding
Study | Warfarin Treated Patients | Control Patients | PT Ratio | INR | % Risk Reduction | p-value | Warfarin Treated Patients | Control Patients
AFASAK | 335 | 336 | 1.5-2.0 | 2.8-4.2 | 60 | 0.027 | 0.6 | 0.0
SPAF | 210 | 211 | 1.3-1.8 | 2.0-4.5 | 67 | 0.01 | 1.9 | 1.9
BAATAF | 212 | 208 | 1.2-1.5 | 1.5-2.7 | 86 | <0.05 | 0.9 | 0.5
CAFA | 187 | 191 | 1.3-1.6 | 2.0-3.0 | 45 | 0.25 | 2.7 | 0.5
SPINAF | 260 | 265 | 1.2-1.5 | 1.4-2.8 | 79 | 0.001 | 2.3 | 1.5
* All study results of warfarin vs. control are based on intention-to-treat analysis and include ischemic stroke and systemic thromboembolism, excluding hemorrhage, and transient ischemic attacks.

Myocardial Infarction

WARIS (The Warfarin Re-Infarction Study) was a double-blind, randomized study of 1214 patients 2 to 4 weeks post-infarction treated with warfarin to a target INR of 2.8 to 4.8. [But note that a lower INR was achieved and increased bleeding was associated with INR's above 4.0; (see DOSAGE AND ADMINISTRATION.)] The primary endpoint was a combination of total mortality and recurrent infarction. A secondary endpoint of cerebrovascular events was assessed. Mean follow-up of the patients was 37 months. The results for each endpoint separately, including an analysis of vascular death, are provided in the following table:

TABLE 3
Event | Warfarin (N=607) | Placebo (N=607) | RR (95%CI) | % Risk Reduction (p-value)
Total Patient Years of Follow-up | 2018 | 1944
Total Mortality | 94 (4.7/100 py) | 123 (6.3/100 py) | 0.76 (0.60, 0.97) | 24 (p=0.030)
Vascular Death | 82 (4.1/100 py) | 105 (5.4/100 py) | 0.78 (0.60,1.02) | 22 (p=0.068)
Recurrent MI | 82 (4.1/100 py) | 124 (6.4/100 py) | 0.66 (0.51, 0.85) | 34 (p=0.001)
Cerebrovascular Event | 20 (1.0/100 py) | 44 (2.3/100 py) | 0.46 (0.28, 0.75) | 54 (p=0.002)
RR=Relative risk; Risk reduction=(I-RR); CI=Confidence Interval; MI=Myocardial Infarction; py=patient years

WARIS II (The Warfarin, Aspirin, Re-Infarction Study) was an open-label randomized study of 3630 patients hospitalized for acute myocardial infarction treated with warfarin target INR 2.8 to 4.2, aspirin 160 mg/day, or warfarin target INR 2.0 to 2.5 plus aspirin 75 mg/day prior to hospital discharge. There were approximately four times as many major bleeding episodes in the two groups receiving warfarin than in the group receiving aspirin alone. Major bleeding episodes were not more frequent among patients receiving aspirin plus warfarin than among those receiving warfarin alone, but the incidence of minor bleeding episodes was higher in the combined therapy group. The primary endpoint was a composite of death, nonfatal reinfarction, or thromboembolic stroke. The mean duration of observation was approximately 4 years. The results for WARIS II are provided in the following table^8:

TABLE 4 WARIS II - DISTRIBUTION OF SEPARATE EVENTS ACCORDING TO TREATMENT GROUP
Event | Aspirin (N=1206) | Warfarin (N=1216) | Aspirin plus Warfarin (N=1208) | Rate Ratio (95% CI)* | p-value
 | No. of Events
Reinfarction | 117 | 90 | 69 | 0.56 (0.41-0.78)a 0.74 (0.55-0.98)b | <0.001 0.03
Thromboembolic stroke | 32 | 17 | 17 | 0.52 (0.28-0.98)a 0.52 (0.28-0.97)b | 0.03 0.03
Major Bleedingc | 8 | 33 | 28 | 3.35a(ND) 4.00b(ND) | ND ND
Minor Bleedingd | 39 | 103 | 133 | 3.21a(ND) 2.55b(ND) | ND ND
Death | 92 | 96 | 95 |  | 0.82
* CI denotes confidence interval.
aThe rate ratio is for aspirin plus warfarin as compared with aspirin.
bThe rate ratio is for warfarin as compared with aspirin.
cMajor bleeding episodes were defined as nonfatal cerebral hemorrhage or bleeding necessitating surgical intervention or blood transfusion.
dMinor bleeding episodes were defined as non-cerebral hemorrhage not necessitating surgical intervention or blood transfusion.
ND =not determined.

Mechanical and Bioprosthetic Heart Valves

In a prospective, randomized, open label, positive-controlled study^9in 254 patients, the thromboembolic-free interval was found to be significantly greater in patients with mechanical prosthetic heart valves treated with warfarin alone compared with dipyridamole-aspirin (p<0.005) and pentoxifylline-aspirin (p<0.05) treated patients. Rates of thromboembolic events in these groups were 2.2, 8.6, and 7.9/100 patient years, respectively. Major bleeding rates were 2.5, 0.0, and 0.9/100 patient years, respectively.

In a prospective, open label, clinical trial comparing moderate (INR 2.65) vs. high intensity (INR 9.0) warfarin therapies in 258 patients with mechanical prosthetic heart valves, thromboembolism occurred with similar frequency in the two groups (4.0 and 3.7 events/100 patient years, respectively). Major bleeding was more common in the high intensity group (2.1 events/100 patient years) vs. 0.95 events/100 patient years in the moderate intensity group.^10

In a randomized trial in 210 patients comparing two intensities of warfarin therapy (INR 2.0-2.25 vs. INR 2.5-4.0) for a three month period following tissue heart valve replacement, thromboembolism occurred with similar frequency in the two groups (major embolic events 2.0% vs. 1.9%, respectively and minor embolic events 10.8% vs. 10.2%, respectively). Major bleeding complications were more frequent with the higher intensity (major hemorrhages 4.6%) vs. none in the lower intensity.^11

INDICATIONS AND USAGE

Warfarin sodium tablets, USP are indicated for the prophylaxis and/or treatment of venous thrombosis and its extension, and pulmonary embolism.

Warfarin sodium tablets, USP are indicated for the prophylaxis and/or treatment of the thromboembolic complications associated with atrial fibrillation and/or cardiac valve replacement.

Warfarin sodium tablets, USP are indicated to reduce the risk of death, recurrent myocardial infarction, and thromboembolic events such as stroke or systemic embolization after myocardial infarction.

CONTRAINDICATIONS

Anticoagulation is contraindicated in any localized or general physical condition or personal circumstance in which the hazard of hemorrhage might be greater than the potential clinical benefits of anticoagulation, such as:

Pregnancy

Warfarin sodium tablets, USP are contraindicated in women who are or may become pregnant because the drug passes through the placental barrier and may cause fatal hemorrhage to the fetusin utero. Furthermore, there have been reports of birth malformations in children born to mothers who have been treated with warfarin during pregnancy.

Embryopathy characterized by nasal hypoplasia with or without stippled epiphyses (chondrodysplasia punctata) has been reported in pregnant women exposed to warfarin during the first trimester. Central nervous system abnormalities also have been reported, including dorsal midline dysplasia characterized by agenesis of the corpus callosum, Dandy-Walker malformation, and midline cerebellar atrophy. Ventral midline dysplasia, characterized by optic atrophy, and eye abnormalities have been observed. Mental retardation, blindness, and other central nervous system abnormalities have been reported in association with second and third trimester exposure. Although rare, teratogenic reports followingin uteroexposure to warfarin include urinary tract anomalies such as single kidney, asplenia, anencephaly, spina bifida, cranial nerve palsy, hydrocephalus, cardiac defects and congenital heart disease, polydactyly, deformities of toes, diaphragmatic hernia, corneal leukoma, cleft palate, cleft lip, schizencephaly, and microcephaly.

Spontaneous abortion and stillbirth are known to occur and a higher risk of fetal mortality is associated with the use of warfarin. Low birth weight and growth retardation have also been reported.

Women of childbearing potential who are candidates for anticoagulant therapy should be carefully evaluated and the indications critically reviewed with the patient. If the patient becomes pregnant while taking this drug, she should be apprised of the potential risks to the fetus, and the possibility of termination of the pregnancy should be discussed in light of those risks.

Hemorrhagic tendencies or blood dyscrasias.

Recent or contemplated surgery of: (1) central nervous system; (2) eye; (3) traumatic surgery resulting in large open surfaces.

Bleeding tendencies associated with active ulceration or overt bleeding of: (1) gastrointestinal, genitourinary or respiratory tracts; (2) cerebrovascular hemorrhage; (3) aneurysms-cerebral, dissecting aorta; (4) pericarditis and pericardial effusions; (5) bacterial endocarditis.

Threatened abortion, eclampsia and preeclampsia.

Inadequate laboratory facilities.

Unsupervised patients with senility, alcoholism, psychosis or other lack of patient cooperation.

Spinal puncture and other diagnostic or therapeutic procedures with potential for uncontrollable bleeding.

Miscellaneous: major regional, lumbar block anesthesia, malignant hypertension and known hypersensitivity to warfarin or to any other components of this product.

WARNINGS

The most serious risks associated with anticoagulant therapy with warfarin sodium are hemorrhage in any tissue or organ^12 (see BLACK BOX WARNING) and, less frequently (<0.1%), necrosis and/or gangrene of skin and other tissues. Hemorrhage and necrosis have in some cases been reported to result in death or permanent disability. Necrosis appears to be associated with local thrombosis and usually appears within a few days of the start of anticoagulant therapy. In severe cases of necrosis, treatment through debridement or amputation of the affected tissue, limb, breast or penis has been reported. Careful diagnosis is required to determine whether necrosis is caused by an underlying disease. Warfarin therapy should be discontinued when warfarin is suspected to be the cause of developing necrosis and heparin therapy may be considered for anticoagulation. Although various treatments have been attempted, no treatment for necrosis has been considered uniformly effective. See below for information on predisposing conditions. These and other risks associated with anticoagulant therapy must be weighed against the risk of thrombosis or embolization in untreated cases.

It cannot be emphasized too strongly that treatment of each patient is a highly individualized matter. Warfarin sodium, a narrow therapeutic range (index) drug, may be affected by factors such as other drugs and dietary vitamin K. Dosage should be controlled by periodic determinations of prothrombin time (PT)/International Normalized Ratio (INR). Determinations of whole blood clotting and bleeding times are not effective measures for control of therapy. Heparin prolongs the one-stage PT. When heparin and warfarin are administered concomitantly, refer below to Conversion From Heparin Therapy for recommendations.

Increased caution should be observed when warfarin is administered in the presence of any predisposing condition where added risk of hemorrhage, necrosis, and/or gangrene is present.

Anticoagulation therapy with warfarin may enhance the release of atheromatous plaque emboli, thereby increasing the risk of complications from systemic cholesterol microembolization, including the "purple toes syndrome." Discontinuation of warfarin therapy is recommended when such phenomena are observed.

Systemic atheroemboli and cholesterol microemboli can present with a variety of signs and symptoms including purple toes syndrome, livedo reticularis, rash, gangrene, abrupt and intense pain in the leg, foot, or toes, foot ulcers, myalgia, penile gangrene, abdominal pain, flank or back pain, hematuria, renal insufficiency, hypertension, cerebral ischemia, spinal cord infarction, pancreatitis, symptoms simulating polyarteritis, or any other sequelae of vascular compromise due to embolic occlusion. The most commonly involved visceral organs are the kidneys followed by the pancreas, spleen, and liver. Some cases have progressed to necrosis or death.

Purple toes syndrome is a complication of oral anticoagulation characterized by a dark, purplish or mottled color of the toes, usually occurring between 3-10 weeks, or later, after the initiation of therapy with warfarin or related compounds. Major features of this syndrome include purple color of plantar surfaces and sides of the toes that blanches on moderate pressure and fades with elevation of the legs; pain and tenderness of the toes; waxing and waning of the color over time. While the purple toes syndrome is reported to be reversible, some cases progress to gangrene or necrosis which may require debridement of the affected area, or may lead to amputation.

Warfarin should be used with caution in patients with heparin-induced thrombocytopenia and deep venous thrombosis. Cases of venous limb ischemia, necrosis, and gangrene have occurred in patients with heparin-induced thrombocytopenia and deep venous thrombosis when heparin treatment was discontinued and warfarin therapy was started or continued. In some patients sequelae have included amputation of the involved area and/or death^13.

The decision to administer anticoagulants in the following conditions must be based upon clinical judgment in which the risks of anticoagulant therapy are weighed against the benefits:

Lactation: Based on very limited published data, warfarin has not been detected in the breast milk of mothers treated with warfarin. The same limited published data report that some breast-fed infants, whose mothers were treated with warfarin, had prolonged prothrombin times, although not as prolonged as those of the mothers. The decision to breast-feed should be undertaken only after careful consideration of the available alternatives. Women who are breast-feeding and anticoagulated with warfarin should be very carefully monitored so that recommended PT/INR values are not exceeded. It is prudent to perform coagulation tests and to evaluate vitamin K status in infants before advising women taking warfarin to breast-feed. Effects in premature infants have not been evaluated.

Severe to moderate hepatic or renal insufficiency.

Infectious diseases or disturbances of intestinal fora: sprue, antibiotic therapy.

Trauma which may result in internal bleeding.

Surgery or trauma resulting in large exposed raw surfaces.

Indwelling catheters.

Severe to moderate hypertension.

Known or suspected deficiency in protein C mediated anticoagulant response: Hereditary or acquired deficiencies of protein C or its cofactor, protein S, have been associated with tissue necrosis following warfarin administration. Not all patients with these conditions develop necrosis, and tissue necrosis occurs in patients without these deficiencies. Inherited resistance to activated protein C has been described in many patients with venous thromboembolic disorders but has not yet been evaluated as a risk factor for tissue necrosis. The risk associated with these conditions, both for recurrent thrombosis and for adverse reactions, is difficult to evaluate since it does not appear to be the same for everyone. Decisions about testing and therapy must be made on an individual basis. It has been reported that concomitant anticoagulation therapy with heparin for 5 to 7 days during initiation of therapy with warfarin may minimize the incidence of tissue necrosis. Warfarin therapy should be discontinued when warfarin is suspected to be the cause of developing necrosis, and heparin therapy may be considered for anticoagulation.

Miscellaneous: polycythemia vera, vasculitis, and severe diabetes.

PRECAUTIONS

Periodic determination of PT/INR is essential. (see DOSAGE AND ADMINISTRATION: Laboratory Control.)

Numerous factors, alone or in combination including changes in diet, medications, botanicals, and genetic variations in the CYP2C9 and VKORC1 enzymes (see CLINICAL PHARMACOLOGY: Pharmacogenomics) may influence the response of the patient to warfarin.

Drug-Drug and Drug-Disease Interactions

It is generally good practice to monitor the patient's response with additional PT/INR determinations in the period immediately after discharge from the hospital, and whenever other medications, including botanicals, are initiated, discontinued or taken irregularly. The following factors are listed for reference; however, other factors may also affect the anticoagulant response.

Drugs may interact with warfarin through pharmacodynamic or pharmacokinetic mechanisms. Pharmacodynamic mechanisms for drug interactions with warfarin are synergism (impaired hemostasis, reduced clotting factor synthesis), competitive antagonism (vitamin K), and altered physiologic control loop for vitamin K metabolism (hereditary resistance). Pharmacokinetic mechanisms for drug interactions with warfarin are mainly enzyme induction, enzyme inhibition, and reduced plasma protein binding. It is important to note that some drugs may interact by more than one mechanism.

The following factors, alone or in combination, may be responsible for INCREASED PT/INR response:

ENDOGENOUS FACTORS:

blood dyscrasias -
seeCONTRAINDICATIONS
cancer
collagen vascular disease
congestive heart failure

diarrhea
elevated temperature
hepatic disorders
infectious hepatitis
jaundice

hyperthyroidism
poor nutritional state
steatorrhea
vitamin K deficiency

EXOGENOUS FACTORS:

Potential drug interactions with warfarin sodium are listed below by drug class and by specific drugs.

Classes of Drugs
5-lipoxygenase Inhibitor Adrenergic Stimulants, Central Alcohol Abuse Reduction Preparations Analgesics Anesthetics, Inhalation Antiandrogen Antiarrhythmics† Antibiotics† Aminoglycosides (oral) Cephalosporins, parenteral Macrolides Miscellaneous Penicillins, intravenous, high dose Quinolones (fluoroquinolones) Sulfonamides, long acting Tetracyclines Anticoagulants Anticonvulsants† Antidepressants† Antimalarial Agents Antineoplastics† Antiparasitic/Antimicrobials | Antiplatelet Drugs/Effects Antithyroid Drugs† Beta-Adrenergic Blockers Cholelitholytic Agents Diabetes Agents, Oral Diuretics† Fungal Medications, Intravaginal, Systemic† Gastric Acidity and Peptic Ulcer Agents† Gastrointestinal Prokinetic Agents Ulcerative Colitis Agents Gout Treatment Agents Hemorrheologic Agents Hepatotoxic Drugs Hyperglycemic Agents Hypertensive Emergency Agents Hypnotics† Hypolipidemics† Bile Acid-Binding Resins† Fibric Acid Derivatives HMG-CoA Reductase Inhibitors† | Leukotriene Receptor Antagonist Monoamine Oxidase Inhibitors Narcotics, prolonged Nonsteroidal Anti- Inflammatory Agents Proton Pump Inhibitors Psychostimulants Pyrazolones Salicylates Selective Serotonin Reuptake Inhibitors Steroids, Adrenocortical† Steroids, Anabolic (17-Alkyl Testosterone Derivatives) Thrombolytics Thyroid Drugs Tuberculosis Agents† Uricosuric Agents Vaccines Vitamins†

Specific Drugs Reported
acetaminophen alcohol† allopurinol aminosalicylic acid amiodarone HCl argatroban aspirin atenolol atorvastatin† azithromycin bivalirudin capecitabine cefamandole cefazolin cefoperazone cefotetan cefoxitin ceftriaxone celecoxib cerivastatin chenodiol chloramphenicol chloral hydrate† chlorpropamide cholestyramine† cimetidine ciprofloxacin cisapride clarithromycin clofibrate cyclophosphamide† danazol dextran dextrothyroxine diazoxide | diclofenac dicumarol diflunisal disulfiram doxycycline erythromycin esomeprazole ethacrynic acid ezetimibe fenofibrate fenoprofen fluconazole fluorouracil fluoxetine flutamide fluvastatin fluvoxamine gefitinib gemifibrozil glucagon halothane heparin ibuprofen ifosfamide indomethacin influenza virus vaccine itraconazole ketoprofen ketorolac lansoprazole lepirudin levamisole levofloxacin levothyroxine liothyronine | lovastatin mefenamic acid methimazole† methyldopa methylphenidate methylsalicylate ointment (topical) metronidazole miconazole (intravaginal, oral, systemic) moricizine hydrochloride† nalidixic acid naproxen neomycin norfloxacin ofloxacin olsalazine omeprazole oxandrolone oxaprozin oxymetholone pantoprazole paroxetine penicillin G, intravenous pentoxifylline phenylbutazone phenytoin† piperacillin piroxicam pravastatin† prednisone† propafenone | propoxyphene propranolol propylthiouracil† quinidine quinine rabeprazole ranitidine† rofecoxib sertraline simvastatin stanozolol streptokinase sulfamethizole sulfamethoxazole sulfinpyrazone sulfisoxazole sulindac tamoxifen tetracycline thyroid ticarcillin ticlopidine tissue plasminogen activator (t-PA) tolbutamide tramadol trimethoprim/ sulfamethoxazole urokinase valdecoxib valproate vitamin E warfarin overdose zafirlukast zileuton
also: other medications affecting blood elements which may modify hemostasis
dietary deficiencies
prolonged hot weather
unreliable PT/INR determinations
†Increased and decreased PT/INR responses have been reported.

The following factors, alone or in combination, may be responsible for DECREASED PT/INR response:

ENDOGENOUS FACTORS:

edema
hereditary coumarin resistance
hyperlipemia

hypothyroidism
nephrotic syndrome

EXOGENOUS FACTORS:

Potential drug interactions with warfarin sodium are listed below by drug class and by specific drugs.

Classes of Drugs
Adrenal Cortical Steroid Inhibitors Antacids Antianxiety Agents Antiarrhythmics† Antibiotics† Anticonvulsants† Antidepressants† Antihistamines Antineoplastics† | Antipsychotic Medications Antithyroid Drugs† Barbiturates Diuretics† Enteral Nutritional Supplements Fungal Medications, Systemic† Gastric Acidity and Peptic Ulcer Agents† Hypnotics† | Hypolipidemics† Bile Acid-Binding Resins† HMG-CoA Reductase Inhibitors† Immunosuppressives Oral Contraceptives, Estrogen Containing Selective Estrogen Receptor Modulators Steroids, Adrenocortical† Tuberculosis Agents† Vitamins†

Specific Drugs Reported
alcohol† aminoglutethimide amobarbital atorvastatin† azathioprine butabarbital butalbital carbamazepine chloral hydrate† chlordiazepoxide chlorthalidone | cholestyramine† clozapine corticotropin cortisone cyclophosphamide† dicloxacillin ethchlorvynol glutethimide griseofulvin haloperidol meprobamate | 6-mercaptopurine methimazole† moricizine hydrochloride† nafcillin paraldehyde pentobarbital phenobarbital phenytoin† pravastatin† prednisone† primidone | propylthiouracil† raloxifene ranitidine† rifampin secobarbital spironolactone sucralfate trazodone vitamin C (high dose) vitamin K warfarin underdosage
also: diet high in vitamin K
unreliable PT/INR determinations
†Increased and decreased PT/INR responses have been reported.

Because a patient may be exposed to a combination of the above factors, the net effect of warfarin sodium on PT/INR response may be unpredictable. More frequent PT/INR monitoring is therefore advisable. Medications of unknown interaction with coumarins are best regarded with caution. When these medications are started or stopped, more frequent PT/INR monitoring is advisable.

It has been reported that concomitant administration of warfarin and ticlopidine may be associated with cholestatic hepatitis.

Botanical (Herbal) Medicines

Caution should be exercised when botanical medicines (botanicals) are taken concomitantly with warfarin. Few adequate, well-controlled studies exist evaluating the potential for metabolic and/or pharmacologic interactions between botanicals and warfarin. Due to a lack of manufacturing standardization with botanical medicinal preparations, the amount of active ingredients may vary. This could further confound the ability to assess potential interactions and effects on anticoagulation. It is good practice to monitor the patient's response with additional PT/INR determinations when initiating or discontinuing botanicals.

Specific botanicals reported to affect warfarin therapy include the following:

- Bromelains, danshen, dong quai (Angelica sinensis), garlic, Ginkgo biloba, ginseng, and cranberry products are associated most often with an INCREASE in the effects of warfarin.
- Coenzyme Q10(ubidecarenone) and St. John's wort are associated most often with a DECREASE in the effects of warfarin.

Some botanicals may cause bleeding events when taken alone (e.g., garlic and Ginkgo biloba) and may have anticoagulant, antiplatelet, and/or fibrinolytic properties. These effects would be expected to be additive to the anticoagulant effects of warfarin. Conversely, other botanicals may have coagulant properties when taken alone or may decrease the effects of warfarin.

Some botanicals that may affect coagulation are listed below for reference; however, this list should not be considered all-inclusive. Many botanicals have several common names and scientific names. The most widely recognized common botanical names are listed.

Botanicals that contain coumarins with potential anticoagulant effects:
Agrimony^1 Alfalfa Angelica (Dong Quai) Aniseed Arnica Asafoetida Bogbean^2 Boldo Buchu Capsicum^3 | Cassia^4 Celery Chamomile (German and Roman) Dandelion^4 Fenugreek Horse Chestnut Horseradish Licorice^4 Meadowsweet^2 Nettle | Parsley Passion Flower Prickly Ash (Northern) Quassia Red Clover Sweet Clover Sweet Woodruff Tonka Beans Wild Carrot Wild Lettuce
Miscellaneous botanicals with anticoagulant properties:
Bladder Wrack(Fucus) | Pau d'arco
Botanicals that contain salicylate and/or have antiplatelet properties:
Agrimony^1 Aloe Gel Aspen Black Cohosh Black Haw Bogbean^2 Cassia^4 Clove | Dandelion^4 Feverfew Garlic^5 German Sarsaparilla Ginger Ginkgo Biloba Ginseng(Panax)^5 Licorice^4 | Meadowsweet^2 Onion^5 Policosanol Poplar Senega Tamarind Willow Wintergreen
Botanicals with fibrinolytic properties:
Bromelains Capsicum^3 | Garlic^5 Ginseng(Panax)^5 | Inositol Nicotinate Onion^5
Botanicals with coagulant properties:
Agrimony^1 | Mistletoe
Goldenseal | Yarrow
^1Contains coumarins, has antiplatelet properties, and may have coagulant properties due to possible Vitamin K content.
^2Contains coumarins and salicylates.
^3Contains coumarins and has fibrinolytic properties.
^4Contains coumarins and has antiplatelet properties.
^5Has antiplatelet and fibrinolytic properties.

Effect on Other Drugs

Coumarins may also affect the action of other drugs. Hypoglycemic agents (chlorpropamide and tolbutamide) and anticonvulsants (phenytoin and phenobarbital) may accumulate in the body as a result of interference with either their metabolism or excretion.

Considerations for Increased Bleeding Risk

Warfarin sodium is a narrow therapeutic range (index) drug, and additional caution should be observed when warfarin sodium is administered to certain patients. Reported risk factors for bleeding include high intensity of anticoagulation (INR >4.0), age ≥65, highly variable INRs, history of gastrointestinal bleeding, hypertension, cerebrovascular disease, serious heart disease, anemia, malignancy, trauma, renal insufficiency, concomitant drugs (see PRECAUTIONS) and long duration of warfarin therapy. Identification of risk factors for bleeding and certain genetic variation in CYP2CP and VKORC1 in a patient may increase the need for more frequent INR monitoring and the use of lower warfarin doses (see CLINICAL PHARMACOLOGY: Metabolism and DOSAGE AND ADMINISTRATION). Bleeding is more likely to occur during the starting period and with a higher dose of warfarin sodium (resulting in a higher INR).

Intramuscular (I.M.) injections of concomitant medications should be confined to the upper extremities which permits easy access for manual compression, inspections for bleeding and use of pressure bandages.

Caution should be observed when warfarin is administered concomitantly with nonsteroidal anti-inflammatory drugs (NSAIDs), including aspirin, to be certain that no change in anticoagulation dosage is required. In addition to specific drug interactions that might affect PT/INR, NSAIDs, including aspirin, can inhibit platelet aggregation, and can cause gastrointestinal bleeding, peptic ulceration and/or perforation.

Information for Patients

The objective of anticoagulant therapy is to decrease the clotting ability of the blood so that thrombosis is prevented, while avoiding spontaneous bleeding. Effective therapeutic levels with minimal complications are in part dependent upon cooperative and well-instructed patients who communicate effectively with their physician. Patients should be advised: Strict adherence to prescribed dosage schedule is necessary. Do not take or discontinue any other medication, including salicylates (e.g., aspirin and topical analgesics), other over-the-counter medications and botanical (herbal) products except on advice of the physician. Avoid alcohol consumption. Do not take warfarin during pregnancy and do not become pregnant while taking it (see CONTRAINDICATIONS). Avoid any activity or sport that may result in traumatic injury. Prothrombin time tests and regular visits to physician or clinic are needed to monitor therapy. Carry identification stating that warfarin is being taken. If the prescribed dose of warfarin is forgotten, notify the physician immediately. Take the dose as soon as possible on the same day but do not take a double dose of warfarin the next day to make up for missed doses. The amount of vitamin K in food may affect therapy with warfarin. Eat a normal, balanced diet maintaining a consistent amount of vitamin K. Avoid drastic changes in dietary habits, such as eating large amounts of green leafy vegetables. You should also avoid intake of cranberry juice or any other cranberry products. Notify your health care provider if any of these products are part of your normal diet. Contact physician to report any illness, such as diarrhea, infection or fever. Notify physician immediately if any unusual bleeding or symptoms occur. Signs and symptoms of bleeding include: pain, swelling or discomfort, prolonged bleeding from cuts, increased menstrual flow or vaginal bleeding, nosebleeds, bleeding of gums from brushing, unusual bleeding or bruising, red or dark brown urine, red or tar black stools, headache, dizziness, or weakness. If therapy with warfarin is discontinued, patients should be cautioned that the anticoagulant effects of warfarin may persist for about 2 to 5 days. Patients should be informed that all warfarin sodium, USP, products represent the same medication, and should not be taken concomitantly, as overdosage may result. A Medication Guide^14should be available to patients when their prescriptions for warfarin sodium are issued

Carcinogenesis, Mutagenesis, Impairment of Fertility

Carcinogenicity and mutagenicity studies have not been performed with warfarin. The reproductive effects of warfarin have not been evaluated. The use of warfarin during pregnancy has been associated with the development of fetal malformations in humans (see CONTRAINDICATIONS).

Use in Pregnancy

Pregnancy Category X - See CONTRAINDICATIONS.

Pediatric Use

Safety and effectiveness in pediatric patients below the age of 18 have not been established in randomized, controlled clinical trials. However, the use of warfarin in pediatric patients is well-documented for the prevention and treatment of thromboembolic events. Difficulty achieving and maintaining therapeutic PT/INR ranges in the pediatric patient has been reported. More frequent PT/INR determinations are recommended because of possible changing warfarin requirements.

Geriatric Use

Patients 60 years or older appear to exhibit greater than expected PT/INR response to the anticoagulant effects of warfarin (see CLINICAL PHARMACOLOGY). Warfarin is contraindicated in any unsupervised patient with senility. Caution should be observed with administration of warfarin sodium to elderly patients in any situation or physical condition where added risk of hemorrhage is present. Lower initiation and maintenance doses of warfarin are recommended for elderly patients (see DOSAGE AND ADMINISTRATION).

ADVERSE REACTIONS

Potential adverse reactions to warfarin may include:

- Fatal or nonfatal hemorrhage from any tissue or organ. This is a consequence of the anticoagulant effect. The signs, symptoms, and severity will vary according to the location and degree or extent of the bleeding. Hemorrhagic complications may present as paralysis; paresthesia; headache, chest, abdomen, joint, muscle or other pain; dizziness; shortness of breath, difficult breathing or swallowing; unexplained swelling; weakness; hypotension; or unexplained shock. Therefore, the possibility of hemorrhage should be considered in evaluating the condition of any anticoagulated patient with complaints which do not indicate an obvious diagnosis. Bleeding during anticoagulant therapy does not always correlate with PT/INR. (See OVERDOSAGE-Treatment.)
- Bleeding which occurs when the PT/INR is within the therapeutic range warrants diagnostic investigation since it may unmask a previously unsuspected lesion, e.g., tumor, ulcer, etc.
- Necrosis of skin and other tissues. (See WARNINGS.)
- Adverse reactions reported infrequently include: hypersensitivity/allergic reactions, including anaphylactic reactions, systemic cholesterol microembolization, purple toes syndrome, hepatitis, cholestatic hepatic injury, jaundice, elevated liver enzymes, hypotension, vasculitis, edema, anemia, pallor, fever, rash, dermatitis, including bullous eruptions, urticaria, angina syndrome, chest pain, abdominal pain including cramping, flatulence/bloating, fatigue, lethargy, malaise, asthenia, nausea, vomiting, diarrhea, pain, headache, dizziness, loss of consciousness, syncope, coma, taste perversion, pruritus, alopecia, cold intolerance, and paresthesia including feeling cold and chills.

Rare events of tracheal or tracheobronchial calcification have been reported in association with long-term warfarin therapy. The clinical significance of this event is unknown.

Priapism has been associated with anticoagulant administration, however, a causal relationship has not been established.

OVERDOSAGE

Signs and Symptoms

Suspected or overt abnormal bleeding (e.g., appearance of blood in stools or urine, hematuria, excessive menstrual bleeding, melena, petechiae, excessive bruising or persistent oozing from superficial injuries) are early manifestations of anticoagulation beyond a safe and satisfactory level.

Treatment

Excessive anticoagulation, with or without bleeding, may be controlled by discontinuing warfarin therapy and if necessary, by administration of oral or parenteral vitamin K1. (Please see recommendations accompanying vitamin K1preparations prior to use.)^15,^16

Such use of vitamin K1reduces response to subsequent warfarin therapy. Patients may return to a pretreatment thrombotic status following the rapid reversal of a prolonged PT/INR. Resumption of warfarin administration reverses the effect of vitamin K, and a therapeutic PT/INR can again be obtained by careful dosage adjustment. If rapid anticoagulation is indicated, heparin may be preferable for initial therapy.

If minor bleeding progresses to major bleeding, give 5 to 25 mg (rarely up to 50 mg) parenteral vitamin K1. In emergency situations of severe hemorrhage, clotting factors can be returned to normal by administering 200 to 500 mL of fresh whole blood or fresh frozen plasma, or by giving commercial Factor IX complex.

A risk of hepatitis and other viral diseases is associated with the use of these blood products; Factor IX complex is also associated with an increased risk of thrombosis. Therefore, these preparations should be used only in exceptional or life-threatening bleeding episodes secondary to warfarin sodium overdosage.

Purified Factor IX preparations should not be used because they cannot increase the levels of prothrombin, Factor VII and Factor X which are also depressed along with the levels of Factor IX as a result of warfarin treatment. Packed red blood cells may also be given if significant blood loss has occurred. Infusions of blood or plasma should be monitored carefully to avoid precipitating pulmonary edema in elderly patients or patients with heart disease.

DOSAGE AND ADMINISTRATION

The dosage and administration of warfarin sodium tablets, USP must be individualized for each patient according to the particular patient's PT/INR response to the drug. The dosage should be adjusted based upon the patient's PT/INR.^15,^16,^17,^18,^19 The best available information supports the following recommendations for dosing of warfarin sodium tablets.

Venous Thromboembolism (including deep venous thrombosis [DVT] and pulmonary embolism [PE])

For patients with a first episode of DVT or PE secondary to a transient (reversible) risk factor, treatment with warfarin for 3 months is recommended. For patients with a first episode of idiopathic DVT or PE, warfarin is recommended for at least 6 to 12 months. For patients with two or more episodes of documented DVT or PE, indefinite treatment with warfarin is suggested. For patients with a first episode of DVT or PE who have documented antiphospholipid antibodies or who have two or more thrombophilic conditions, treatment for 12 months is recommended and indefinite therapy is suggested. For patients with a first episode of DVT or PE who have documented deficiency of antithrombin, deficiency of Protein C or Protein S, or the Factor V Leiden or prothrombin 20210 gene mutation, homocystinemia, or high Factor VIII levels (>90th percentile of normal), treatment for 6 to 12 months is recommended and indefinite therapy is suggested for idiopathic thrombosis. The risk-benefit should be reassessed periodically in patients who receive indefinite anticoagulant treatment.^12,^20The dose of warfarin should be adjusted to maintain a target INR of 2.5 (INR range, 2.0 to 3.0) for all treatment durations. These recommendations are supported by the 7th ACCP guidelines.^(15, 17, 21, 22)

Atrial Fibrillation

Five clinical trials evaluated the effects of warfarin in patients with non-valvular atrial fibrillation (AF). Meta-analysis findings of these studies revealed that the effects of warfarin in reducing thromboembolic events including stroke were similar at either moderately high INR (2.0-4.5) or low INR (1.4-3.0). There was a significant reduction in minor bleeds at the low INR. There are no adequate and well-controlled studies in populations with atrial fibrillation and valvular heart disease. Similar data from clinical studies in valvular atrial fibrillation patients are not available. The trials in non-valvular atrial fibrillation support the American College of Chest Physicians' (7th ACCP) recommendation that an INR of 2.0-3.0 be used for warfarin therapy in appropriate AF patients.^17

Oral anticoagulation therapy with warfarin is recommended in patients with persistent or paroxysmal AF (PAF) (intermittent AF) at high risk of stroke (i.e., having any of the following features: prior ischemic stroke, transient ischemic attack, or systemic embolism, age >75 years, moderately or severely impaired left ventricular systolic function and/or congestive heart failure, history of hypertension, or diabetes mellitus). In patients with persistent AF or PAF, age 65 to 75 years, in the absence of other risk factors, but who are at intermediate risk of stroke, antithrombotic therapy with either oral warfarin or aspirin, 325 mg/day, is recommended. For patients with AF and mitral stenosis, anticoagulation with oral warfarin is recommended (7th ACCP). For patients with AF and prosthetic heart valves, anticoagulation with oral warfarin should be used; the target INR may be increased and aspirin added depending on valve type and position, and on patient factors.^17

Post-Myocardial Infarction

The results of the WARIS II study and 7th ACCP guidelines suggest that in most healthcare settings, moderate- and low-risk patients with a myocardial infarction should be treated with aspirin alone over oral vitamin-K antagonist (VKA) therapy plus aspirin. In healthcare settings in which meticulous INR monitoring is standard and routinely accessible, for both high- and low-risk patients after myocardial infarction (MI), long-term (up to 4 years) high-intensity oral warfarin (target INR, 3.5; range, 3.0 to 4.0) without concomitant aspirin or moderate-intensity oral warfarin (target INR, 2.5; range, 2.0 to 3.0) with aspirin is recommended. For high-risk patients with MI, including those with a large anterior MI, those with significant heart failure, those with intracardiac thrombus visible on echocardiography, and those with a history of a thromboembolic event, therapy with combined moderate-intensity (INR, 2.0 to 3.0) oral warfarin plus low-dose aspirin (≤100 mg/day) for 3 months after the MI is suggested.^23

Mechanical and Bioprosthetic Heart Valves

For all patients with mechanical prosthetic heart valves, warfarin is recommended. For patients with a St. Jude Medical (St. Paul, MN) bileaflet valve in the aortic position, a target INR of 2.5 (range, 2.0 to 3.0) is recommended. For patients with tilting disk valves and bileaflet mechanical valves in the mitral position, the 7th ACCP recommends a target INR of 3.0 (range, 2.5 to 3.5). For patients with caged ball or caged disk valves, a target INR of 3.0 (range, 2.5 to 3.5) in combination with aspirin, 75 to 100 mg/day is recommended. For patients with bioprosthetic valves, warfarin therapy with a target INR of 2.5 (range, 2.0 to 3.0) is recommended for valves in the mitral position and is suggested for valves in the aortic position for the first 3 months after valve insertion.^15

Recurrent Systemic Embolism and Other Indications

Oral anticoagulation therapy has not been evaluated by properly designed clinical trials in patients with valvular disease associated with atrial fibrillation, patients with mitral stenosis, and patients with recurrent systemic embolism of unknown etiology. A moderate dose regimen (INR 2.0 to 3.0) is recommended for these patients.^17

An INR of greater than 4.0 appears to provide no additional therapeutic benefit in most patients and is associated with a higher risk of bleeding.

Initial Dosage

The dosing of warfarin sodium tablets, USP must be individualized according to patient's sensitivity to the drug as indicated by the PT/INR. Use of a large loading dose may increase the incidence of hemorrhagic and other complications, does not offer more rapid protection against thrombi formation, and is not recommended. It is recommended that warfarin sodium tablets, USP therapy be initiated with a dose of 2 to 5 mg per day with dosage adjustments based on the results of PT/INR determinations.^17,18The lower initiation doses should be considered for patients with certain genetic variations in CYP2C9 and VKORC1 enzymes as well as for elderly and/or debilitated patients and patients with potential to exhibit greater than expected PT/INR responses to warfarin sodium (see CLINICAL PHARMACOLOGY and PRECAUTIONS).

Maintenance

Most patients are satisfactorily maintained at a dose of 2 to 10 mg daily. Flexibility of dosage is provided by breaking scored tablets in half. The individual dose and interval should be gauged by the patient's prothrombin response. Acquired or inherited warfarin resistance is rare, but should be suspected if large daily doses of warfarin sodium tablets, USP are required to maintain a patient's PT/INR within a normal therapeutic range. Lower maintenance doses are recommended for elderly and/or debilitated patients and patients with a potential to exhibit greater than expected PT/INR response to warfarin sodium tablets, USP (see PRECAUTIONS).

Duration of Therapy

The duration of therapy in each patient should be individualized. In general, anticoagulant therapy should be continued until the danger of thrombosis and embolism has passed.^(14, 15, 17, 18, 21, 22)

Missed Dose

The anticoagulant effect of warfarin sodium tablets, USP persists beyond 24 hours. If the patient forgets to take the prescribed dose of warfarin sodium tablets, USP at the scheduled time, the dose should be taken as soon as possible on the same day. The patient should not take the missed dose by doubling the daily dose to make up for missed doses, but should refer back to his or her physician.

Laboratory Control

The PT reflects the depression of vitamin K dependent Factors VII, X and II. A system of standardizing the PT in oral anticoagulant control was introduced by the World Health Organization in 1983. It is based upon the determination of an International Normalized Ratio (INR) which provides a common basis for communication of PT results and interpretations of therapeutic ranges.^24 The PT should be determined daily after the administration of the initial dose until PT/INR results stabilize in the therapeutic range. Intervals between subsequent PT/INR determinations should be based upon the physician's judgment of the patient's reliability and response to warfarin sodium tablets, USP in order to maintain the individual within the therapeutic range. Acceptable intervals for PT/INR determinations are normally within the range of one to four weeks after a stable dosage has been determined. To ensure adequate control, it is recommended that additional PT tests be done when other warfarin products are interchanged with warfarin sodium tablets, USP, as well as whenever other medications are initiated, discontinued, or taken irregularly (see PRECAUTIONS).Safety and efficacy of warfarin therapy can be improved by increasing the quality of laboratory control. Reports suggest that in usual care monitoring, patients are in therapeutic range only 33%-64% of the time. Time in therapeutic range is significantly greater (56%-93%) in patients managed by anticoagulation clinics, among self-testing and self-monitoring patients, and in patients managed with the help of computer programs.^25Self-testing patients had fewer bleeding events than patients in usual care.^25

Treatment During Dentistry and Surgery

The management of patients who undergo dental and surgical procedures requires close liaison between attending physicians, surgeons and dentists.^(15, 19)PT/INR determination is recommended just prior to any dental or surgical procedure. In patients undergoing minimal invasive procedures who must be anticoagulated prior to, during, or immediately following these procedures, adjusting the dosage of warfarin sodium tablets, USP to maintain the PT/INR at the low end of the therapeutic range may safely allow for continued anticoagulation. The operative site should be sufficiently limited and accessible to permit the effective use of local procedures for hemostasis. Under these conditions, dental and minor surgical procedures may be performed without undue risk of hemorrhage. Some dental or surgical procedures may necessitate the interruption of warfarin therapy. When discontinuing warfarin even for a short period of time, the benefits and risks should be strongly considered.

Conversion from Heparin Therapy

Since the anticoagulant effect of warfarin sodium tablets, USP is delayed, heparin is preferred initially for rapid anticoagulation. Conversion to warfarin sodium tablets, USP may begin concomitantly with heparin therapy or may be delayed 3 to 6 days. To ensure continuous anticoagulation, it is advisable to continue full dose heparin therapy and that warfarin sodium tablets, USP therapy be overlapped with heparin for 4 to 5 days, until warfarin sodium tablets, USP has produced the desired therapeutic response as determined by PT/INR. When warfarin sodium tablets, USP has produced the desired PT/INR or prothrombin activity, heparin may be discontinued.

Warfarin sodium tablets, USP may increase the activated partial thromboplastin time (aPTT) test, even in the absence of heparin. A severe elevation (>50 seconds) in activated partial thromboplastin time (aPTT) with a PT/INR in the desired range has been identified as an indication of increased risk of postoperative hemorrhage.

During initial therapy with warfarin sodium tablets, USP, the interference with heparin anticoagulation is of minimal clinical significance.

As heparin may affect the PT/INR, patients receiving both heparin and warfarin sodium tablets, USP should have blood for PT/INR determination drawn at least:

- 5 hours after the last IV bolus dose of heparin, or
- 4 hours after cessation of a continuous IV infusion of heparin, or
- 24 hours after the last subcutaneous heparin injection.

HOW SUPPLIED

Repackaged by Aphena Pharma Solutions - TN.
See Repackaging Information for available configurations.

Warfarin Sodium Tablets, USP: For oral use, single scored, imprinted numerically and packaged with potencies, colors and engravings as follows:

 |  |  | Bottles of (using NDC 60429-)
Mg | Color | Imprint | 15 | 20 | 25 | 30 | 35 | 40 | 45 | 50 | 60 | 75 | 90 | 100 | 1000 | 100 10×10 Blister pks
1 | Pink | 1 | 784-15 |  |  | 784-30 |  |  | 784-45 |  |  |  |  | 784-01 | 784-10 | 784-77
2 | Lavender | 2 | 785-15 |  |  | 785-30 | 785-35 | 785-40 | 785-45 |  | 785-60 |  |  | 785-01 | 785-10 | 785-77
2.5 | Green | 2 1/2 | 786-15 |  |  | 786-30 |  |  | 786-45 |  |  |  |  | 786-01 | 786-10 | 786-77
3 | Tan | 3 | 787-15 |  |  | 787-30 |  |  | 787-45 |  |  |  |  | 787-01 | 787-10 | 787-77
4 | Blue | 4 | 788-15 |  |  | 788-30 |  |  | 788-45 |  |  |  |  | 788-01 | 788-10 | 788-77
5 | Peach | 5 | 789-15 | 789-15 | 789-25 | 789-30 | 789-35 | 789-40 | 789-45 | 789-50 | 789-60 | 789-75 | 789-90 | 789-01 | 789-10 | 789-77
6 | Teal | 6 | 790-15 |  |  | 790-30 |  |  | 790-45 |  |  |  |  | 790-01 | 790-10 | 790-77
7.5 | Yellow | 7 1/2 | 791-15 |  |  | 791-30 |  |  | 791-45 |  |  |  |  | 791-01 | 791-10 | 791-77
10 | White | 10 | 792-15 |  |  | 792-30 |  |  | 792-45 |  |  |  |  | 792-01 |  | 792-77

Warfarin Sodium Tablets, USP are available in 1, 2, 2.5, 3, 4, 5, 6, 7.5 and 10 mg of warfarin sodium, USP. They are flat beveled capsule shaped tablets, scored and engraved as described in the above table on one side, and engraved with "WARFARIN" on top of "TARO" on the other side.

Storage

Store at 20-25° C (68-77° F) [see USP Controlled Room Temperature]. Protect from light. Dispense in a tight, light-resistant container as defined in the USP.

REFERENCES

1. Yasar U, Eliasson E, Dahl M, Johansson I, Ingelman-Sundberg M, Sjoqvist F. Validation of methods for CYP2C9 genotyping: Frequencies of mutant alleles in Swedish population.Biochem Biophys Res Comm. 1999;254:628-631.
2. Herman D, Locatelli I, Grabnar I, et al. Influence of CYP2C9 polymorphisms, demographic factors and concomitant drug therapy on warfarin metabolism and maintenance dose.Pharmacogenomics J. 2005;5:193-202.
3. Sanderson S, Emery J, Higgins J. CYP2C9 gene variants, drug dose, and bleeding risk in warfarin-treated patients: A HuGEnet™ systemic review and meta-analysis.Genet Med. 2005;7:97-104.
4. Lindh JD, Lundgren S, Holm L, Alfredsson L, Rane A. Several-fold increase in risk of overanticoagulation by CYP2C9 mutations.Clin Pharmacol Ther. 2005;78:540-550.
5. Wadelius M, Chen LY, Downes K, et al. Common VKORC1 and GGCX polymorphisms associated with warfarin dose.Pharmacogenomics J. 2005;5:262-270.
6. Veenstra DL, You JHS, Rieder MJ, et al. Association of Vitamin K epoxide reductase complex 1 (VKO-RC1) variants with warfarin dose in a Hong Kong Chinese patient population.Pharmacogenet Genomics. 2005;15:687-691.
7. Takahashi H, Wilkinson GR, Nutescu EA, et al. Different contributions of polymorphisms in VKORC1 and CYP2C9 to intra- and inter-population differences in maintenance doses of warfarin in Japanese, Caucasians and African Americans.Pharmacogenet Genomics. 2006;16:101-110.
8. Hurlen M, Abdelnoor M, Smith P, Erikssen J, Arnesen H. Warfarin, aspirin, or both after myocardial infarction.N Engl J Med. 2002;347:969-974.
9. Mok CK, Boey J, Wang R, et al. Warfarin versus dipyridamole-aspirin and pentoxifylline-aspirin for prevention of prosthetic valve thromboembolism: a prospective randomized clinical trial.Circ. 1985;72:1059-1063.
10. Saour JN, Sieck JO, Mamo LA, Gallus AS. Trial of different intensities of anticoagulation in patients with prosthetic heart valves.N Engl J Med. 1990;322:428-432.
11. Turpie AG, Hirsh J, Gunstensen J, Nelson H, Gent M. Randomized comparison to two intensities of oral anticoagulant therapy after tissue heart valve replacement.Lancet. 1988;331:1242-1245.
12. Büller HR, Agnelli G, Hull RD, Hyers TM, Prins MH, Raskob GE. Antithrombotic Therapy for Venous Thromboembolic Disease. The Seventh ACCP Conference on Antithrombotic and Thrombolytic Therapy.Chest. 2004;126:401S-428S.
13. Warkentin TE, Elavathil LJ, Hayward CPM, Johnston MG, Russett JI, Kelton JG. The pathogenesis of venous limb gangrene associated with heparin-induced thrombocytopenia.Ann Intern Med. 1997;127:804-812.
14. COUMADIN Medication Guide. Princeton, NJ: Bristol-Myers Squibb Company; 2007.
15. Salem DN, Stein PD, Al-Ahmad A, et al. Antithrombotic therapy in valvular heart disease–native and prosthetic. The Seventh ACCP Conference on Antithrombotic and Thrombolytic Therapy.Chest. 2004;126:457S-482S.
16. American Geriatrics Society Clinical Practice Guidelines. The use of oral anticoagulants (warfarin) in older people.J Amer Geriatr Soc. 2000;48:224-227.
17. Singer DE, Albers GW, Dalen JE, Go AS, Halperin JL, Manning WJ. Antithrombotic therapy in atrial fibrillation. The Seventh ACCP Conference on Antithrombotic and Thrombolytic Therapy.Chest. 2004;126:429S-456S.
18. Jaffer AK, Bragg L. Practical tips for warfarin dosing and monitoring.Cleveland Clinic J Med. 2003;70:361-371.
19. Jaffer AK, Brotman DJ, Chukwumerije N. When patients on warfarin need surgery.Cleveland Clinic J Med. 2003;70:973-984.
20. Kearon C, Ginsberg JS, Kovacs MJ, et al, for the Extended Low-Intensity Anticoagulation for Thrombo-Embolism Investigators. Comparison of low-intensity warfarin therapy with conventional-intensity warfarin therapy for longterm prevention of recurrent venous thromboembolism.N Engl J Med. 2003;349:631-639.
21. Schulman S, Granqvist S, Holmström M, et al, and the Duration of Anticoagulation Trial Study Group. The duration of oral anticoagulant therapy after a second episode of venous thromboembolism.N Engl J Med. 1997;336:393-398.
22. Ridker PM, Goldhaber SZ, Danielson E, et al, for the PREVENT Investigators. Long-term, low-intensity warfarin therapy for the prevention of recurrent venous thromboembolism.N Engl J Med. 2003;348:1425-1434.
23. Harrington RA, Becker RC, Ezekowitz M, et al. Antithrombotic therapy for coronary artery disease. The Seventh ACCP Conference on Antithrombotic and Thrombolytic Therapy.Chest. 2004;126:513S-548S.
24. Ansell J, Hirsh J, Pollen L, Bussey H, Jacobson A, Hylek E. The pharmacology and management of the vitamin K antagonists. The Seventh ACCP Conference on Antithrombotic and Thrombolytic Therapy.Chest. 2004;126:204S-233S.
25. Heneghan C, Alonso-Coello P, Garcia-Alamino JM, Perera R, Meats E, Glasziou P. Self-monitoring of oral anticoagulation: a systematic review and meta-analysis.Lancet. 2006;367:404-411.

Mfd. by: Taro Pharmaceutical Industries Ltd., Haifa Bay, Israel 26110
Marketed/Packaged for: GSMS, Inc. Camarillo, CA 93012

MEDICATION GUIDE

Warfarin Sodium Tablets, USP Crystalline

Read this Medication Guide before you start taking Warfarin Sodium (WARFARIN) and each time you get a refill. There may be new information. This Medication Guide does not take the place of talking to your healthcare provider about your medical condition or treatment. You and your healthcare provider should talk about WARFARIN when you start taking it and at regular checkups.

What is the most important information I should know about WARFARIN?

- Take your WARFARIN exactly as prescribed to lower the chance of blood clots forming in your body.(See "What is WARFARIN?").
- Warfarin is very important for your health, but it can cause serious and life-threatening bleeding problems. To benefit from WARFARIN and also lower your chance for bleeding problems, you must:
  - Get your regular blood test to check for your response to WARFARIN. This blood test is called a PT/INR test. The PT/INR test checks to see how fast your blood clots. Your healthcare provider will decide what PT/INR numbers are best for you. Your dose of WARFARIN will be adjusted to keep your PT/INR in a target range for you.
  - Call your healthcare provider right away if you get any of the following signs or symptoms of bleeding problems:
    - pain, swelling or discomfort
    - headaches, dizziness, or weakness
    - unusual bruising (bruises that develop without known cause or grow in size)
    - nose bleeds
    - bleeding gums
    - bleeding from cuts takes a long time to stop
    - menstrual bleeding or vaginal bleeding that is heavier than normal
    - pink or brown urine
    - red or black stools
    - coughing up blood
    - vomiting blood or material that looks like coffee grounds
- Many other medicines, including prescription and non-prescription medicines, vitamins and herbal supplements can interact with WARFARIN and: Tell your healthcare provider about all the medicines, vitamins and herbal supplements you take. Do not stop medicines or take anything new unless you have talked to your healthcare provider. Keep a list of your medicines with you at all times to show your healthcare provider and pharmacist.
  - affect the dose you need, or
  - increase WARFARIN side effects.
- Do not take other medicines that contain warfarin. Warfarin is the active ingredient in WARFARIN.
- Some foods can interact with WARFARIN and affect your treatment and dose.
  - Eat a normal, balanced diet. Talk to your doctor before you make any diet changes. Do not eat large amounts of leafy green vegetables. Leafy green vegetables contain Vitamin K. Certain vegetable oils also contain large amounts of Vitamin K. Too much Vitamin K can lower the effect of WARFARIN.
  - Avoid drinking cranberry juice or eating cranberry products.
  - Avoid drinking alcohol.
- Always tell all of your healthcare providers that you take WARFARIN.
- Wear or carry information that you take WARFARIN.

What is WARFARIN?

WARFARIN is an anticoagulant medicine. It is used to lower the chance of blood clots forming in your body. Blood clots can cause a stroke, heart attack, or other serious conditions such as blood clots in the legs or lungs.

Who should not take WARFARIN?

Do not take WARFARIN if:

- your chance of having bleeding problems is higher than the possible benefit of treatment. Your healthcare provider will decide if WARFARIN is right for you. Talk to your healthcare provider about all of your health conditions.
- you are pregnant or plan to become pregnant. WARFARIN can cause death or birth defects to an unborn baby. Use effective birth control if you can get pregnant.
- you are allergic to warfarin or to anything else in WARFARIN.

What should I tell my healthcare provider before starting WARFARIN?

Tell your healthcare provider about all of your health conditions, including if you:

- have bleeding problems
- fall often
- have liver or kidney problems
- have high blood pressure
- have a heart problem called congestive heart failure
- have diabetes
- drink alcohol or have problems with alcohol abuse. Alcohol can affect your WARFARIN dose and should be avoided.
- are pregnant or planning to become pregnant. See "Who should not take WARFARIN?"
- are breastfeeding. Warfarin Sodium Tablets may increase bleeding in your baby. Talk to your doctor about the best way to feed your baby. If you choose to breastfeed while taking WARFARIN, both you and your baby should be carefully monitored for bleeding problems.

Tell your healthcare provider about all the medicines you take including prescription and non-prescription medicines, vitamins, and herbal supplements. See "What is the most important information I should know about WARFARIN?"

How should I take WARFARIN?

- Take WARFARIN exactly as prescribed. Your healthcare provider will adjust your dose from time to time depending on your response to WARFARIN.
- You must have regular blood tests and visits with your healthcare provider to monitor your condition.
- Take WARFARIN at the same time every day. You can take WARFARIN either with food or on an empty stomach.
- If you miss a dose of WARFARIN, call your healthcare provider. Take the dose as soon as possible on the same day. Do not take a double dose of WARFARIN the next day to make up for a missed dose.
- Call your healthcare provider right away if you take too many WARFARIN.
- Call your healthcare provider if you are sick with diarrhea, an infection, or have a fever.
- Tell your healthcare provider about any planned surgeries, medical or dental procedures. Your WARFARIN may have to be stopped for a short time or you may need your dose adjusted.
- Call your healthcare provider right away if you fall or injure yourself, especially if you hit your head. Your healthcare provider may need to check you.

What should I avoid while taking WARFARIN?

- Do not start, stop, or change any medicine without talking with your healthcare provider.
- Do not make changes in your diet, such as eating large amounts of green, leafy vegetables.
- Do not change your weight by dieting, without first checking with your healthcare provider.
- Avoid drinking alcohol.
- Do not do any activity or sport that may cause a serious injury.

What are the possible side effects of WARFARIN?

- WARFARIN is very important for your health, but it can cause serious and life-threatening bleeding problems. See "What is the most important information I should know about WARFARIN?"
- Serious side effects of WARFARIN also include:
  - death of skin tissue (skin necrosis or gangrene). This can happen soon after starting WARFARIN. It happens because blood clots form and block blood flow to an area of your body. Call your healthcare provider right away if you have pain, color, or temperature change to any area of your body. You may need medical care right away to prevent death or loss (amputation) of your affected body part.
  - "purple toes syndrome". Call your healthcare provider right away if you have pain in your toes and they look purple in color or dark in color.

Other side effects with WARFARIN include allergic reactions, liver problems, low blood pressure, swelling, low red blood cells, paleness, fever, and rash. Call your healthcare provider if you have any side effect that bothers you.

These are not all of the side effects of WARFARIN. For more information, ask your healthcare provider or pharmacist.

How should I store WARFARIN?

- Store WARFARIN at room temperature between 68° and 77° F. Protect from light.
- Keep WARFARIN and all medicines out of the reach of children.

General Information about WARFARIN

Medicines are sometimes prescribed for purposes not mentioned in a Medication Guide. Do not use WARFARIN for a condition for which it was not prescribed. Do not give WARFARIN to other people, even if they have the same condition. It may harm them.

This Medication Guide summarizes the most important information about WARFARIN. If you would like more information, talk with your healthcare provider. You can ask your healthcare provider or pharmacist for information about WARFARIN that was written for healthcare professionals.

If you would like more information, call 1-800-544-1449.

Rx only

Mfd. by: Taro Pharmaceutical Industries Ltd., Haifa Bay, Israel 26110

Marketed/Packaged by: GSMS, Inc. Camarillo, CA 93012

This Medication Guide has been approved by the U.S. Food and Drug Administration.

January 2009

Repackaging Information

Please reference the How Supplied section listed above for a description of individual tablets or capsules. This drug product has been received by Aphena Pharma - TN in a manufacturer or distributor packaged configuration and repackaged in full compliance with all applicable cGMP regulations. The package configurations available from Aphena are listed below:

Count | 2mg
15 | 67544-318-15
30 | 67544-318-30
35 | 67544-318-35
40 | 67544-318-40
45 | 67544-318-45
50 | 67544-318-50
60 | 67544-318-53
70 | 67544-318-61
75 | 67544-318-55
90 | 67544-318-60
120 | 67544-318-70

Count | 1mg | 2.5mg | 3mg | 4mg | 5mg | 6mg | 7.5mg | 10mg
15 | - | - | - | - | 43353-050-15 | - | - | -
20 | - | - | - | - | 43353-050-20 | - | - | -
25 | - | - | - | - | 43353-050-25 | - | - | -
26 | - | - | - | - | 43353-050-68 | - | - | -
28 | - | - | - | - | 43353-050-28 | - | - | -
30 | 43353-584-30 | 43353-142-30 | 43353-089-30 | 43353-049-30 | 43353-050-30 | 43353-587-30 | 43353-579-30 | 43353-578-30
34 | - | - | - | - | 43353-050-78 | - | - | -
35 | - | - | - | - | 43353-050-35 | - | - | -
40 | - | 43353-142-40 | - | - | 43353-050-40 | - | - | -
45 | - | 43353-142-45 | - | - | 43353-050-45 | - | - | -
50 | - | - | - | - | 43353-050-50 | - | - | -
55 | - | - | - | - | 43353-050-38 | - | - | -
60 | - | 43353-142-53 | - | - | 43353-050-53 | - | - | -
70 | - | - | - | - | 43353-050-61 | - | - | -
75 | - | - | - | - | 43353-050-55 | - | - | -
80 | - | - | - | - | 43353-050-57 | - | - | -
90 | 43353-584-60 | 43353-142-60 | 43353-089-60 | 43353-049-60 | 43353-050-60 | - | - | -
100 | - | - | - | - | 43353-050-65 | - | - | -
120 | - | - | - | - | 43353-050-70 | - | - | -
9000 | - | - | - | - | - | - | 43353-579-09 | 43353-578-09

Store between 20°-25°C (68°-77°F). See USP Controlled Room Temperature. Dispense in a tight light-resistant container as defined by USP. Keep this and all drugs out of the reach of children.

Repackaged by:
Cookeville, TN 38506
20140506SC

PRINCIPAL DISPLAY PANEL - 2mg

NDC 67544-318 - Warfarin Sodium 2mg - Rx Only